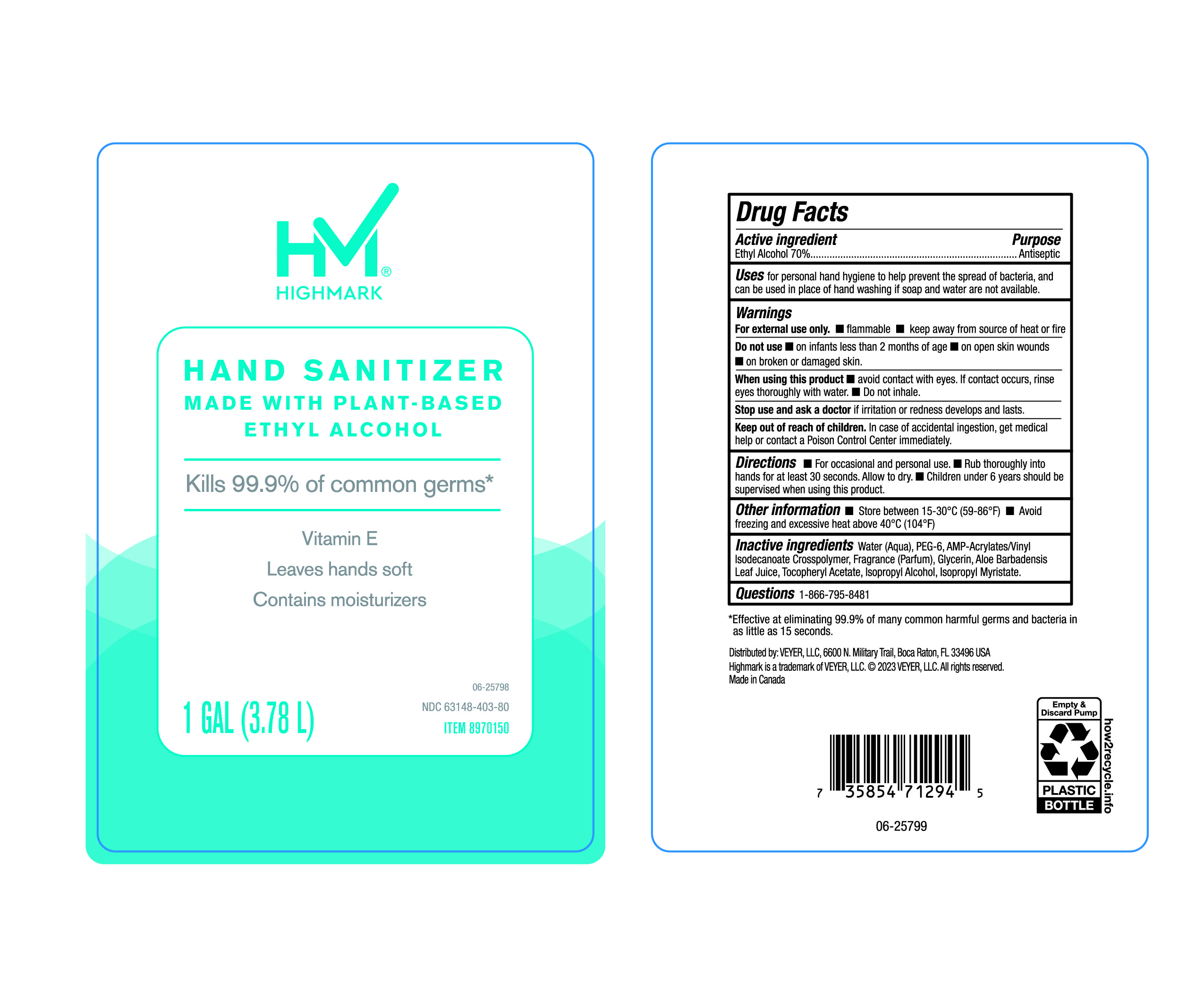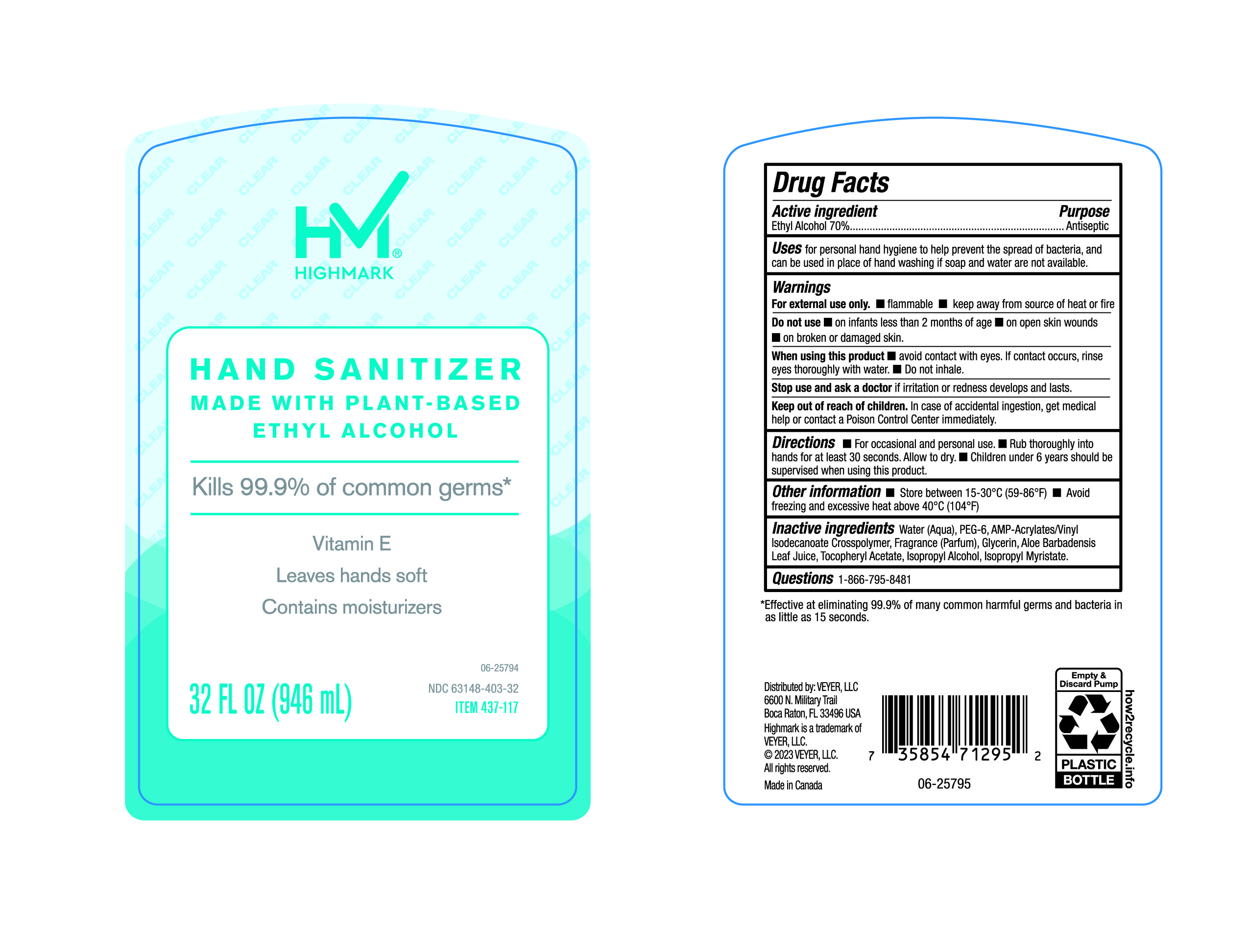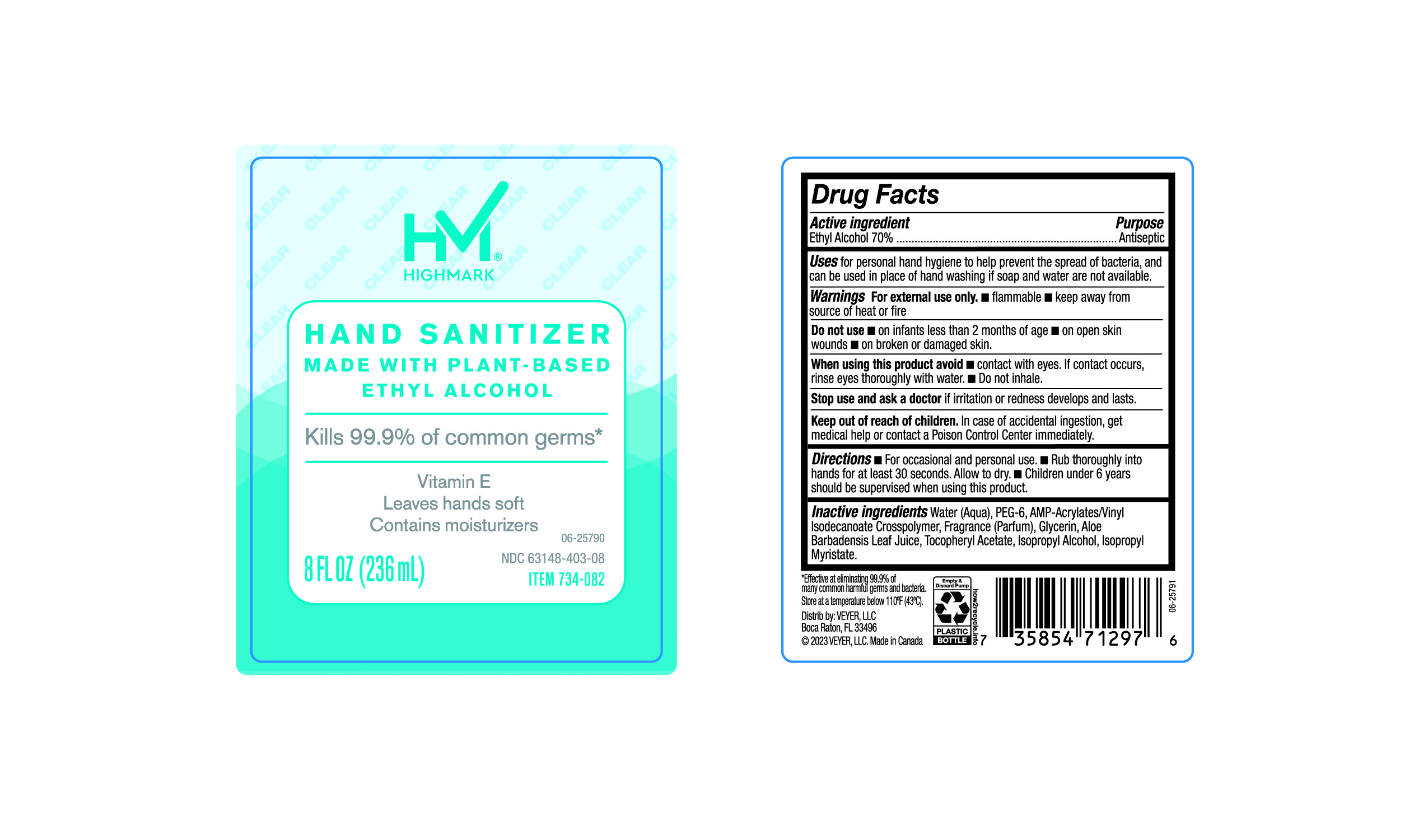 DRUG LABEL: HIMARK
NDC: 63148-403 | Form: LIQUID
Manufacturer: Apollo Health and Beauty Care
Category: otc | Type: HUMAN OTC DRUG LABEL
Date: 20241020

ACTIVE INGREDIENTS: ALCOHOL 70 mL/100 mL
INACTIVE INGREDIENTS: ALOE VERA LEAF; WATER; FRAGRANCE CLEAN ORC0600327; .ALPHA.-TOCOPHEROL ACETATE; ISOPROPYL MYRISTATE; GLYCERIN; ISOPROPYL ALCOHOL; POLYETHYLENE GLYCOL 300; ACRYLATES/VINYL ISODECANOATE CROSSPOLYMER (10000 MPA.S NEUTRALIZED AT 0.5%)

63148-403, HiMark Hand Sanitizer

Active Ingredient

Ethyl Alcohol 70%

Purpose

Antiseptic

Uses

For personal hand hygiene to help prevent the spread of bacteria, and can be used in place of hand washing if soap and water are not available.

Warnings

For external use only.

- Flammable
- Keep away from source of heat or fire.

Do not use

- On infants less than 2 months of age.
- On open skin wounds
- On broken or damaged skin.

When using this product

- Avoid contact with eyes. If contact occurs, rinse eyes thoroughly with water.
- Do not inhale.

Stop use and ask a doctor

if irritation or redness develops and lasts.

Keep out of reach of children

In case of accidental ingestion, get medical help or contact a Poison Control Center immediately.

Directions

- For occassional and Personal use.
- Rub thoroughly into hands for at least 30 seconds. Allow to dry.
- Children under 6 years should be supervised when using this product.

Other Information.

- Store between 15-30°C (59-86°F)
- Avoid freezing and excessive heat above 40°C (104°F)

Inactive Ingredients

Water (Aqua), PEG-6, AMP-Acrylates/vinyl Isodecanoate Crosspolymer, Fragrance (Parfum), Glycerin, Aloe Barbadensis Leaf Juice, Tocopheryl Acetate, Isopropyl Alcohol, Isopropyl Myristate.

Questions?

1-866-795-8481